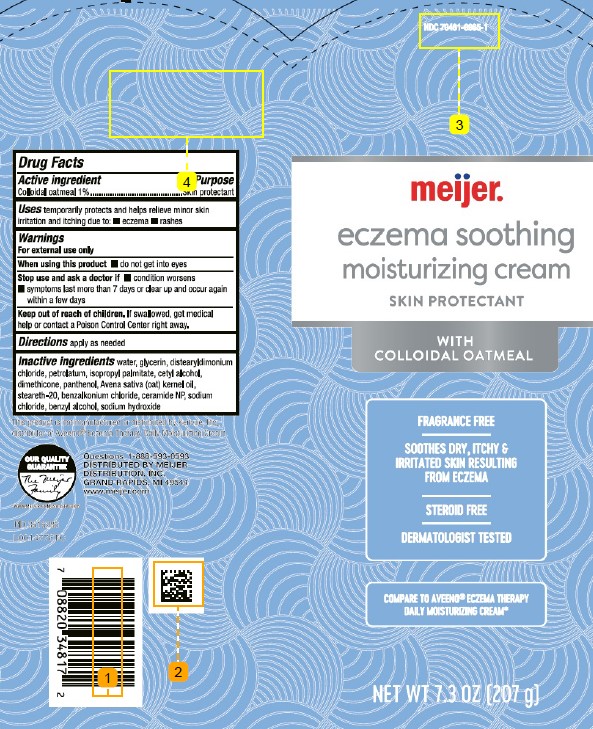 DRUG LABEL: Colloidal oatmeal
NDC: 79481-9965 | Form: CREAM
Manufacturer: Meijer, Inc.
Category: otc | Type: HUMAN OTC DRUG LABEL
Date: 20260224

ACTIVE INGREDIENTS: OATMEAL 10 mg/1 g
INACTIVE INGREDIENTS: WATER; GLYCERIN; DISTEARYLDIMONIUM CHLORIDE; PETROLATUM; ISOPROPYL PALMITATE; CETYL ALCOHOL; DIMETHICONE; PANTHENOL; OAT KERNEL OIL; STEARETH-20; BENZALKONIUM CHLORIDE; CERAMIDE 3; SODIUM CHLORIDE; BENZYL ALCOHOL; SODIUM HYDROXIDE

Meijer 965.001/965AC
Eczema Soothing Moisturizing Cream

Active ingredient

Colloidal oatmeal 1%

Purpose

Skin protectant

Uses

temporarily protects and helps relieve minor skin irritation and itching due to:

- eczema
- rashes

Warnings

For external use only

When using this product

- do not get into eyes

Stop use and ask a doctor if

- condition worsens
- symptoms last more than 7 days or clear up and occur again within a few days

Keep out of reach of children.

If swallowed, get medical help or contact a Poison Control Center right away.

Directions

apply as needed

Inactive ingredients

water, glycerin, distearyldimonium chloride, petrolatum, isopropyl palmitate, cetyl alcohol, dimethicone, panthenol, Avena sativa (oat) kernel oil, steareth-20, benzalkonium chloride, ceramide NP, sodium chloride, benzyl alcohol, sodium hydroxide

Disclaimer

*This product is not manufactured or distributed by Kenvue, Inc., distributor of Aveeno®Eczema Therapy Moisturizing Cream.

ADVERSE REACTION

OUR QUALITY GUARANTEE

The Meijer Family

www.meijer.com/satisfaction

Questions 1-888-593-0593

DISTRIBUTED BY

MEIJER DISTRIBUTION, INC.

GRAND RAPIDS, MI 49544

www.meijer.com

Principal Panel Display

NDC 79481-9965-1

Meijer

eczema soothing

MOISTURIZING CREAM

Skin Protectant

with Colloidal Oatmeal

Fragrance free

Soothes dry, itchy & irritated skin resulting from eczema

Steroid free

Dermatologist tested

Compare to Aveeno®Eczema Therapy Daily Moisturizing Cream*

NET WT 7.3 OZ (207 g)